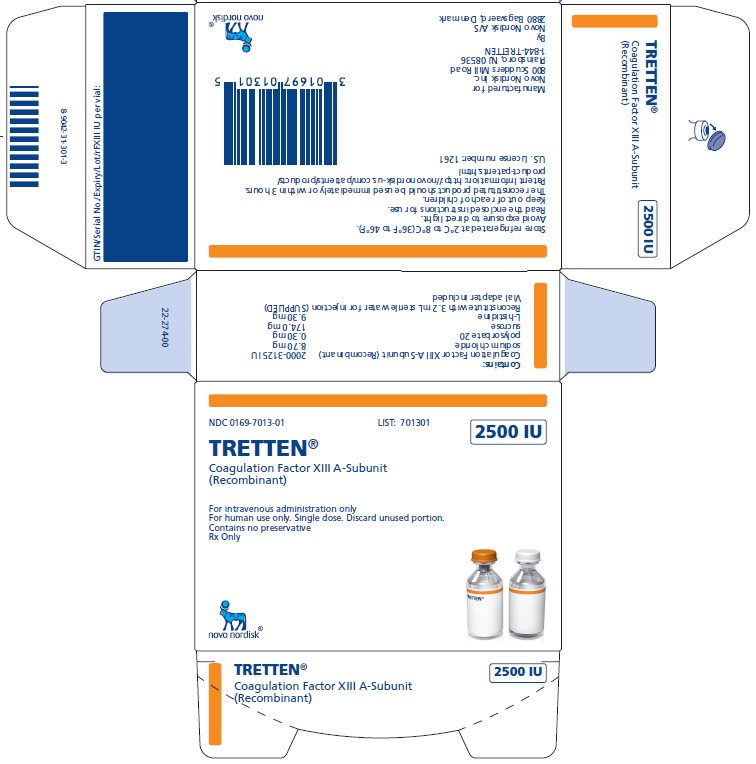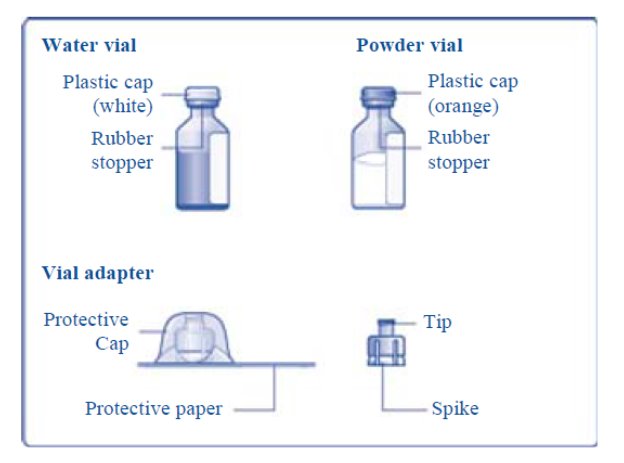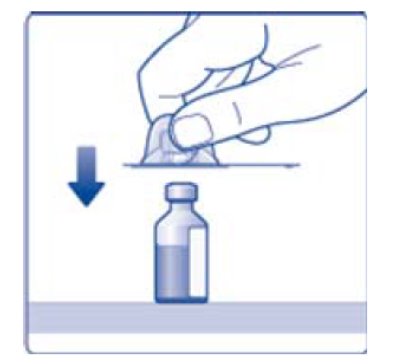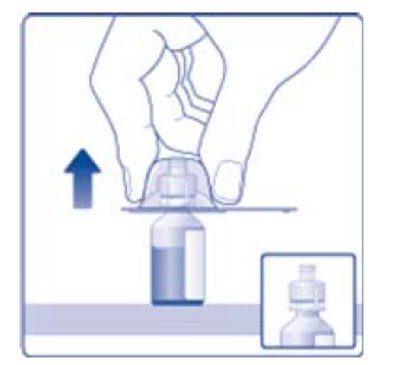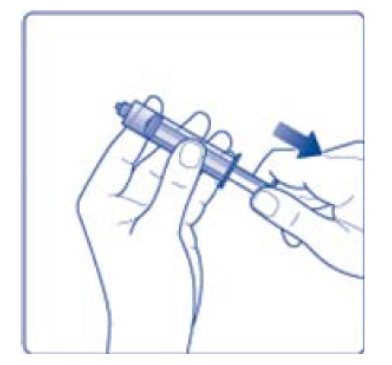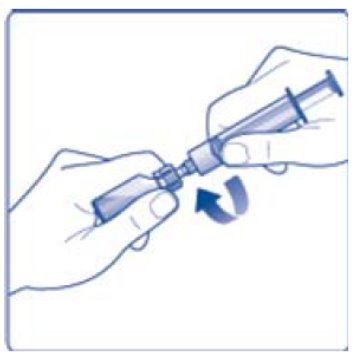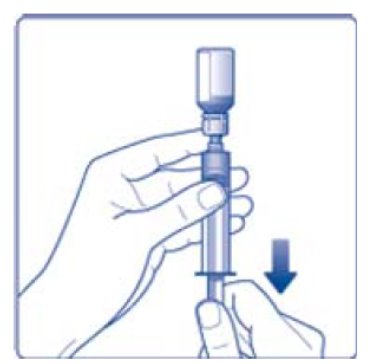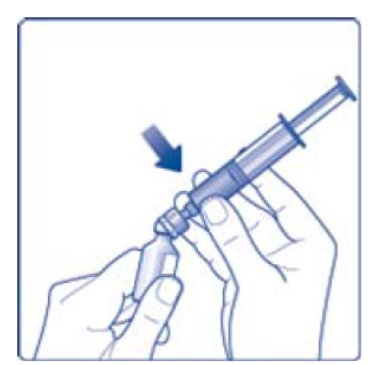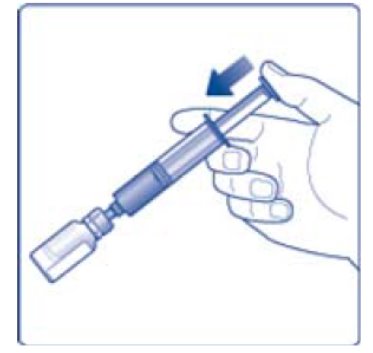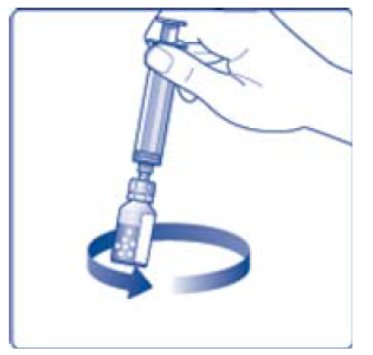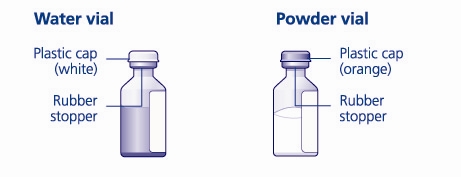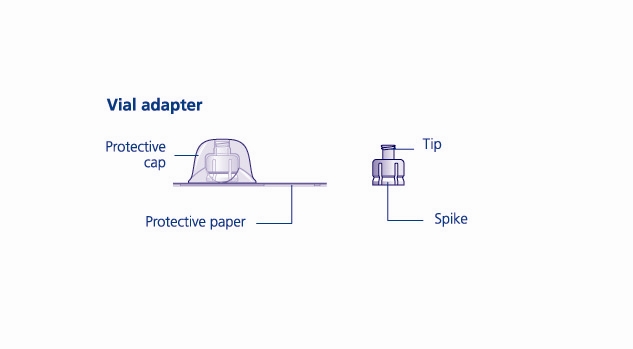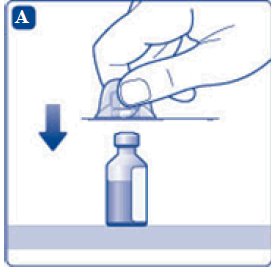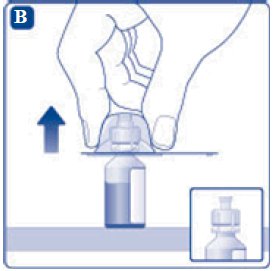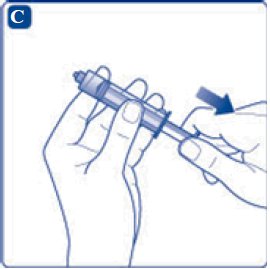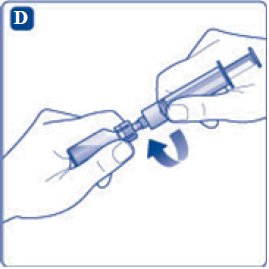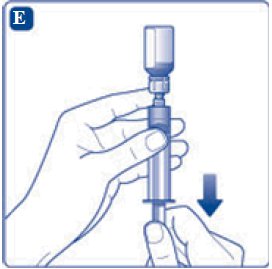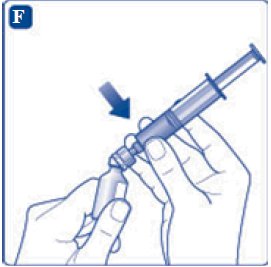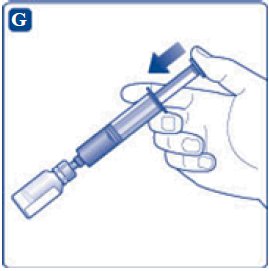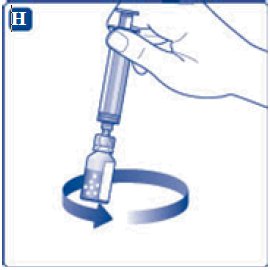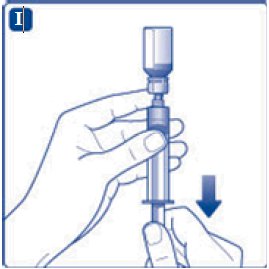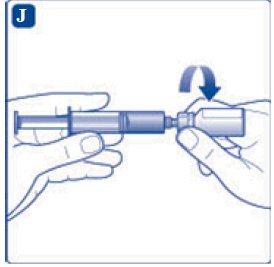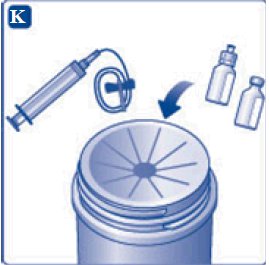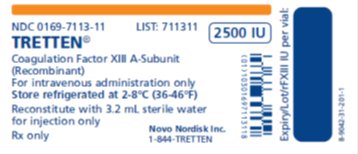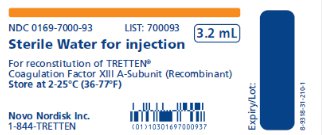 DRUG LABEL: TRETTEN
NDC: 0169-7013 | Form: KIT | Route: INTRAVENOUS
Manufacturer: Novo Nordisk
Category: other | Type: PLASMA DERIVATIVE
Date: 20200630

ACTIVE INGREDIENTS: CATRIDECACOG 2500 [iU]/3 mL
INACTIVE INGREDIENTS: SODIUM CHLORIDE 8.7 mg/3 mL; SUCROSE 174 mg/3 mL; POLYSORBATE 20 0.30 mg/3 mL; HISTIDINE 9.30 mg/3 mL; WATER 3.2 mL/1 mL

HIGHLIGHTS OF PRESCRIBING INFORMATION

These highlights do not include all the information needed to use TRETTEN safely and effectively. See full prescribing information for TRETTEN.
TRETTEN, Coagulation Factor XIII A-Subunit (Recombinant)
For Intravenous Use. Lyophilized Powder for Solution for Injection
Initial U.S. Approval: 2013

1 INDICATIONS AND USAGE

TRETTEN, Coagulation Factor XIII A-Subunit (Recombinant), is indicated for routine prophylaxis of bleeding in patients with congenital factor XIII A-subunit deficiency. (1)

TRETTEN is not for use in patients with congenital factor XIII B‑subunit deficiency. (1)

2 DOSAGE AND ADMINISTRATION

For intravenous use only.

Dose:

- 35 international units per kilogram body weight once monthly to achieve a target trough level of FXIII activity at or above 10% using a validated assay. (2.1)
- Consider dose adjustment if adequate coverage is not achieved with a 35 IU/kg dose. (2.1)
- Once reconstituted, TRETTEN may be diluted with 0.9% sodium chloride to facilitate measurement of small volumes. (2.2)

Rate: Do not exceed 1-2 mL per minute. (2.3)

3 DOSAGE FORMS AND STRENGTHS

- Lyophilized powder in single-dose vial containing 2000 - 3125 IU of recombinant coagulation factor XIII A-subunit.
- After reconstitution with 3.2 mL of sterile water for injection, each vial contains 667-1042 IU/mL of recombinant coagulation factor XIII A-subunit.

4 CONTRAINDICATIONS

Hypersensitivity to the active substance or to any of the excipients. (4)

5 WARNINGS AND PRECAUTIONS

- Discontinue if allergic or hypersensitivity reactions occur. (5.1)
- Monitor patients for thrombosis. (5.2)
- Analyze for neutralizing antibodies if FXIII activity fails to reach expected levels or if reduced therapeutic effect is observed. (5.3)

6 ADVERSE REACTIONS

The most common adverse reactions reported in the clinical trials (≥1%) were headache, pain in the extremities, injection site pain, D dimer increase. (6)

To report SUSPECTED ADVERSE REACTIONS, contact Novo Nordisk Inc. at 1-844-873-8836 or FDA at 1-800-FDA-1088 or www.fda.gov/medwatch

7 DRUG INTERACTIONS

Do not administer TRETTEN with recombinant factor VIIa. (7)

FULL PRESCRIBING INFORMATION

1 INDICATIONS AND USAGE

TRETTEN, Coagulation Factor XIII A-Subunit (Recombinant), is indicated for routine prophylaxis for bleeding in patients with congenital factor XIII A-subunit deficiency.

TRETTEN is not for use in patients with congenital factor XIII B‑subunit deficiency

2 DOSAGE AND ADMINISTRATION

For intravenous use only.

2.1 Dose

- Treatment should be initiated under the supervision of a physician experienced in the treatment of rare bleeding disorders.
- The dose for routine prophylaxis for bleeding in patients with congenital factor XIII (FXIII) A-subunit deficiency is 35 international units (IU) per kilogram body weight once monthly to achieve a target trough level of FXIII activity at or above 10% using a validated assay.
- Consider dose adjustment if adequate coverage is not achieved with the recommended 35 IU/kg dose.
A pharmacokinetic study was conducted in the FXIII congenitally deficient population evaluating five dose cohorts (2, 7, 24, 60 and 89 IU/kg) with blood sampling at 0.5, 1, 4, 8, 24, 48, 72 hours, and 7, 14, and 28 days. Samples were tested for FXIII activity by a chromogenic assay and for FXIII A2B2 tetramer levels by an ELISA, as well as for other analytes. It was found that FXIII tetramer levels were proportional to the observed FXIII activity up to the point of replacement of 100% of normal FXIII activity, but there was no increase in FXIII tetramer levels at higher levels of FXIII activity. A dose of 35 IU/kg is sufficient to replace 100% of FXIII activity in this population, and higher doses may not increase the levels of tetrameric Factor XIII.

2.2 Reconstitution

Reconstitute only with sterile water for injection (provided with TRETTEN). The product can be reconstituted using the vial adapter included or a needle.

Reconstitute using the following procedures:

1. Use aseptic technique.
2. Wash hands before starting.
3. Bring TRETTEN (white lyophilized powder) and sterile water for injection (diluent) to room temperature, but not above 25°C (77°F).
4. Remove the plastic caps from the two vials.
5. Clean the rubber stoppers on the vials with sterile alcohol swabs and allow them to dry before use.
6. Remove the protective paper from the vial adapter, but do not unscrew the protective cap. Attach the vial adapter to the diluent vial, without taking the vial adapter out of the protective cap. Once attached, remove the protective cap from the vial adapter by lightly squeezing the protective cap with your thumb and index finger as shown on the figure below.

7. Draw back the plunger of the sterile syringe and admit a volume of 3.2 mL air into the syringe.

8. Screw the syringe onto the vial adapter on the diluent vial.

9. Inject the air from the syringe into the diluent vial until resistance is felt. Then hold the syringe with the diluent vial upside down and withdraw 3.2 mL water into the syringe.

10. Remove the empty diluent vial by tipping the syringe with the attached vial adapter.

11. Attach the syringe with the vial adapter to the powder vial. Hold the syringe slightly tilted with vial facing downwards. Push the plunger slowly to inject all water (3.2 mL) into the powder vial. Do not inject the diluent directly on the TRETTEN powder to avoid foaming.

12. Gently swirl the vial until all material is dissolved. Do not shake the vial. The reconstituted TRETTEN is a clear and colorless solution. Use the reconstituted TRETTEN immediately. If not, store the solution refrigerated or at room temperature not to exceed 25°C (77°F) for up to three hours. Discard after three hours.

NOTE:

- For larger dose that requires multiple vials of TRETTEN, reconstitute each additional vial using the same procedure with a separate syringe.
- For smaller dose that requires less than the full volume in the vial, reconstituted TRETTEN may be diluted with 0.9% sodium chloride to facilitate measurement of small volumes. Discard remaining product.
- For home administration, any such changes should be communicated by the pharmacist or healthcare provider to the patient or family.

2.3 Administration

- Inspect the reconstituted TRETTEN visually for particulate matter and discoloration prior to administration. Do not use if particulate matter or discoloration is observed.
- Administer at a rate not exceeding 1-2 mL per minute.
- Do not administer with other infusion solutions.
- Do not administer as drip.

3 DOSAGE FORMS AND STRENGTHS

TRETTEN, Coagulation Factor XIII A-Subunit (Recombinant), is available as a white lyophilized powder in single-dose vial containing nominally 2500 IU per vial (2000 – 3125 IU) of recombinant coagulation factor XIII A-subunit. The actual amount of TRETTEN in IU is stated on each carton and vial.

After reconstitution with the provided Sterile Water for Injection, each vial contains 667-1042 IU/mL recombinant coagulation factor XIII A-subunit.

4 CONTRAINDICATIONS

TRETTEN is contraindicated in patients who have known hypersensitivity to the active substance or to any of the excipients [See Description (11)].

5 WARNINGS AND PRECAUTIONS

5.1 Hypersensitivity Reactions

TRETTEN may cause allergic reactions. If signs or symptoms of anaphylaxis or hypersensitivity reactions (including urticaria, rash, tightness of the chest, wheezing, hypotension) occur, discontinue immediately and institute appropriate treatment.

5.2 Thromboembolic Risk

Thromboembolic complications may occur. Monitor patients with conditions that predispose to thrombosis for signs and symptoms of thrombosis after administration of TRETTEN.

5.3 Inhibitors

Inhibitory antibodies may occur with TRETTEN. Patients with inhibitory antibodies may manifest as an inadequate response to treatment. If expected plasma FXIII activity levels are not attained, or if breakthrough bleeding occurs while receiving prophylaxis, perform an assay that measures FXIII inhibitory antibody concentrations.

6 ADVERSE REACTIONS

The most common adverse reactions reported in clinical trials (≥1%), were headache, pain in the extremities, injection site pain, and increase in fibrin D dimer levels.

6.1 Clinical Trials Experience

Because clinical trials are conducted under widely varying conditions, adverse reaction rates observed in the clinical trials of a drug cannot be directly compared to rates in the clinical trials of another drug and may not reflect the rates observed in practice.

During clinical development, TRETTEN was administered to 77 subjects with congenital factor XIII A-subunit deficiency (3:2, male: female ratio) for a total of 1990 doses. Fifty subjects (65%) were between the ages of 18 and 77 years (received 1338 doses), 21 subjects (27%) were between the ages of 6 and less than 18 years old (received 560 doses), and 6 subjects (8%) were less than 6 years old (received 92 doses). Subjects were exposed for up to 4.5 years.

Of the 77 subjects, 68 received 1979 monthly doses of 35 IU/kg of TRETTEN for routine prophylaxis of bleeding. Eleven single doses of TRETTEN have been administered to nine subjects for pharmacokinetic investigations.

The adverse drug reactions reported included headache, pain in the extremities, pain at the injection site, and increase in fibrin D dimer levels (without evidence of thromboembolic events).

Immunogenicity

The detection of antibody formation is highly dependent on the sensitivity and specificity of the assay. Additionally, the observed incidence of antibody (including neutralizing antibody) positivity in an assay may be influenced by several factors including assay methodology, sample handling, timing of sample collection, concomitant medications, and underlying disease. For these reasons, comparison of the incidence of antibodies to TRETTEN with the incidence of antibodies to other products may be misleading.

Transient non-neutralizing antibodies were seen in one out of 50 healthy subjects after one dose, four out of 77 trial subjects (age < 18 years) with congenital factor XIII A-subunit deficiency after one or two doses (3 discontinued from the trial), and in one subject (age < 18 years) in a post marketing safety study after 3.5 years of treatment. In two subjects, the non-neutralizing antibodies disappeared after continued treatment with TRETTEN. In all cases, the non-neutralizing antibodies were found to be of no clinical significance. No subjects developed neutralizing antibodies (inhibitors) against TRETTEN during clinical trials.

7 DRUG INTERACTIONS

Thrombosis may occur if TRETTEN is administered concomitantly with factor VIIa [See Nonclinical Pharmacology (13.2)].

8 USE IN SPECIFIC POPULATIONS

8.1 Pregnancy

Risk Summary

There are no adequate and well-controlled studies using TRETTEN in pregnant women to determine whether there is a drug-associated risk. Animal reproduction studies have not been conducted with TRETTEN.

In the U.S. general population, the estimated background risk of major birth defects and miscarriage in clinically recognized pregnancies is 2-4% and 15-20%, respectively.

Miscarriage is a known complication of congenital FXIII deficiency. Pooling data from 39 publications, the miscarriage rate was 66% in 63 patients with 192 pregnancies (70% in 179 pregnancies in FXIII A-subunit deficiency women). Miscarriage rate was 91% in the 136 pregnancies without routine prophylaxis with FXIII concentrates and 11% in the 45 pregnancies treated with routine FXIII prophylaxis^2.

8.2 Lactation

Risk Summary

There is no information regarding the presence of TRETTEN in human milk, the effect on the breastfed infant, and the effects on milk production. The developmental and health benefits of breastfeeding should be considered along with the mother’s clinical need for TRETTEN and any potential adverse effects on the breastfed infant from TRETTEN or from the underlying maternal condition.

8.4 Pediatric Use

Pediatric subjects in the phase 3 study and the extension study included 6 children in the age range 0-5, 12 children in the age range 6-12, and 9 adolescents in the age range 13-17 who were treated with TRETTEN for a total of 652 exposures. Adverse reactions were more frequently reported in subjects aged from 6 to less than 18 years old than in adults; a greater number of possible/probably trial drug related events were reported in the subjects below 18 years of age (6 subjects with 11 events in 27 enrolled subjects) than in those above 18 years (3 subjects with 3 events in 41 enrolled subjects). Three subjects under 18 years experienced non-neutralizing antibodies and were withdrawn from the study. A fourth pediatric subject who had a non-neutralizing antibody remained in the trial. No dose adjustment is required for pediatric age group.

8.5 Geriatric Use

The safety and efficacy of TRETTEN in the geriatric population have not been established due to an insufficient number of patients.

10 OVERDOSAGE

One subject accidentally received a dose 2.3 times the recommended dose. No clinical signs and symptoms were observed.

11 DESCRIPTION

TRETTEN, Coagulation Factor XIII A-Subunit (Recombinant), is a recombinant human factor XIII-A2 homodimer composed of two factor XIII (FXIII) A-subunits. The FXIII A-subunit is a 731 amino acid chain with an acetylated N-terminal serine. When FXIII is activated by thrombin, a 37 amino acid peptide is cleaved from the N-terminus of the A‑subunit.

TRETTEN is manufactured as an intracellular, soluble protein in yeast (Saccharomyces cerevisiae) production strain containing the episomal expression vector, pD16. It is subsequently isolated by homogenization of cells and purification by several chromatography steps, including hydrophobic interaction and ion exchange chromatography. No human or animal derived products are used in the manufacturing process.

TRETTEN is supplied as a sterile, white lyophilized powder in a single-dose vial. Table 1 and Table 2 list the vial content of reconstituted TRETTEN and the diluent, respectively.

Table 1 Content of Reconstituted TRETTEN*
Content | Per Vial* | Function
Coagulation Factor XIII A-Subunit (Recombinant) | 2000 - 3125 IU | Active substance
Sodium Chloride | 8.70 mg | Stabilizer
Sucrose | 174.0 mg | Stabilizer
Polysorbate 20 | 0.30 mg | Surfactant
L-Histidine | 9.30 mg | Buffer

*Values are given per 3 mL reconstituted TRETTEN.

Table 2 Content of Diluent for Reconstitution of TRETTEN
Content | Per Vial | Function
Sterile Water for Injection | 3.2 mL | Diluent

After reconstitution with 3.2 mL sterile water for injection, each vial contains 667-1042 IU/mL of recombinant coagulation factor XIII A-subunit. The reconstituted solution has a pH of approximately 8.0. The formulation contains no preservative and must only be administered intravenously.

12 CLINICAL PHARMACOLOGY

12.1 Mechanism of Action

FXIII is the terminal enzyme in the blood coagulation cascade. When activated by thrombin at the site of vessel wall injury, FXIII plays an important role in the maintenance of hemostasis through cross-linking of fibrin and other proteins in the fibrin clot.

In plasma, FXIII circulates as a heterotetramer [A2B2] composed of two FXIII A-subunits and two FXIII B-subunits held together by strong non-covalent interactions. The FXIII A is the catalytic subunit and FXIII B-subunit acts as carrier molecule for the FXIII A-subunit in circulation, and is present in excess in plasma. When FXIII A-subunit is bound to FXIII B-subunit [A2B2] the half-life of the FXIII A-subunit [A2] is prolonged. FXIII is a pro-enzyme (protransglutaminase), which is activated by thrombin in the presence of Ca^2+. The enzymatic activity resides with the FXIII A-subunit. Upon activation, the FXIII A‑subunit dissociates from the FXIII B-subunit and thereby exposes the active site of the FXIII A-subunit. The active transglutaminase cross-links fibrin and other proteins resulting in increased mechanical strength and resistance to fibrinolysis of the fibrin clot and contributes to enhance platelet and clot adhesion to injured tissue.

Coagulation Factor XIII A-Subunit (Recombinant) is a protransglutaminase (rFXIII [rA2] homodimer) and binds to free human FXIII B-subunit resulting in a heterotetramer [rA2B2] with a similar half-life to [A2B2]. rFXIII has been shown to be activated by thrombin in the presence of Ca^2+. Activated rFXIII has been shown in dose-dependent manner to increase mechanical strength of fibrin clots, retard fibrinolysis, and rFXIII has been shown to enhance platelet adhesion to the site of injury. After combining with available plasma B-subunits, Coagulation Factor XIII A-subunit (Recombinant) has been shown to have the same pharmacodynamic properties in plasma as endogenous FXIII.

12.2 Pharmacodynamics

A qualitative assay of clot solubility is widely used as an indicator of FXIII deficiency; when performed correctly the test is positive only when the FXIII activity in the sample is close to zero. The results of standard coagulation tests are normal as it is the quality of the clot that is affected. In addition, at present there are no markers that can quantitatively assess the in vivo pharmacodynamics of FXIII.

12.3 Pharmacokinetics

Steady State in Subjects with Congenital Factor XIII Deficiency

In 23 subjects with congenital FXIII A-subunit deficiency on prophylaxis, the pharmacokinetics of rFXIII were evaluated over a dosing interval of 28 days during steady state.

The pharmacokinetic parameters based on steady state baseline adjusted FXIII activity (Berichrom assay) values are shown in Table 3.

Table 3 Pharmacokinetic parameters based on steady state baseline adjusted FXIII activity

Parameters | Mean (SD)
Css, max (IU/mL) | 0.71 (0.17)
Css, min (IU/mL) | 0.05 (0.05)
AUC(0-inf) (IU*h/mL) | 128.3 (40.5)
Clearance (mL/h/kg) | 0.33 (0.11)
Half-life (days) | 5.1 (2.6)
Vss (mL/kg) | 65.9 (26.9)
MRT (days) | 7.9 (3.4)

At steady state, the pharmacokinetics of rFXIII are comparable with the single dose pharmacokinetics of rFXIII.

Pediatric (Ages 1 to < 6 Years Old)

In a pharmacokinetic trial six children with congenital FXIII A-subunit deficiency on prophylaxis treatment were administered a single intravenous dose of 35 IU/kg. The pharmacokinetic parameters based on baseline adjusted FXIII activity (Berichrom assay) values are shown in Table 4. No dose adjustment is needed for pediatric patients as there is no influence of age on the pharmacokinetics of TRETTEN.

Table 4 The pharmacokinetic parameters based on baseline adjusted FXIII activity

Parameters | Mean (SD)
Cmax (IU/mL) | 0.48 (0.14)
AUC(0-inf) (IU*h/mL) | 107.8 (32.2)
Clearance (mL/h/kg) | 0.41 (0.20)
Half-life (days) | 7.1 (1.9)
Vss (mL/kg) | 61.2 (41.0)
MRT (days) | 7.5 (4.8)

13 NONCLINICAL TOXICOLOGY

13.1 Carcinogenesis, Mutagenesis, Impairment of Fertility

Long-term studies in animals to evaluate the carcinogenic potential of TRETTEN, or studies to determine the effects of TRETTEN on genotoxicity or fertility have not been performed. An assessment of the carcinogenic potential of TRETTEN was completed and suggests minimal carcinogenic risk from product use.

13.2 Animal Toxicology and/or Pharmacology

Exaggerated pharmacologic effects, including general thrombosis, ischemic necrosis and mortality were observed in nonclinical studies with TRETTEN and non-proteolytically activated recombinant FXIII at a dose of 1670 IU/kg, i.e., 48 times the recommended human dose of 35 IU/kg.

In a monkey cardiovascular safety pharmacology model evaluating the combination of excessive doses of TRETTEN (585 IU/kg, 17 times the expected human dose) in combination with rFVIIa (1000 mcg/kg, 11 times the expected human dose), one of the twelve monkeys died 4 hours after treatment due to thrombosis. Procoagulant risk factors, including 6 indwelling catheters per monkey and the induction of anesthesia, may have complicated the study results. It is unclear whether the mortality was related to the overdose of one or both products, or a specific interaction between them. Nonclinical and clinical studies with the combination of TRETTEN and rFVIIa at recommended human doses have not been performed.

14 CLINICAL STUDIES

To establish the efficacy of TRETTEN for the prevention of bleeding in patients with congenital FXIII A-subunit deficiency, a multi-center, open-label, non-controlled trial was conducted for 52 weeks in forty-one (41) subjects ≥ 6 years. All subjects received monthly doses of TRETTEN at 35 IU/kg. Bleeding episodes that required treatment with a FXIII-containing product were observed to evaluate the efficacy of monthly replacement therapy with TRETTEN on prevention of bleeding episodes.

Subjects with congenital FXIII A-subunit deficiency confirmed by genotyping were included. Subjects who before entering the trial had received regular replacement therapy were to have initiated regular replacement therapy at least 6 months prior to screening and were to have a documented history of at least one treatment-requiring bleeding episode before initiation of regular replacement therapy or a documented family history of FXIII congenital deficiency. Subjects who before entering the trial had only received on-demand treatment were to have a documented history of at least two treatment-requiring bleeding episodes within 12 months of the screening visit. Severe bleeders as defined by a documented history of ≥2 treatment requiring bleedings per year during regular FXIII replacement therapy were excluded.

During the prophylaxis treatment period with TRETTEN (434 subject months), five bleeding episodes treated with FXIII-containing products were observed in four subjects. All five were associated with trauma. When calculated for all 41 subjects, this translated into a mean annual rate of bleeding episodes that required treatment of 0.14 [95% CI:0.058- 0.332] per subject year, which was statistically significantly lower than the historic bleeding rate of 1.68 per subject year for on-demand treatment. The age-adjusted rate of bleeding episodes that required treatment during the TRETTEN treatment period was 0.05 [95% CI: 0.0094 - 0.2501] per subject year with a model-based estimate corresponding to the mean age of 26.4 years. The mean annual bleeding rate in subjects below 18 years of age was higher compared to that in adults (0.362 versus 0.040 bleeds/subject/year). Table 5 below lists the estimated bleeding rates by age.

Table 5 Estimated Bleeding Rates by Age

Group | N | Estimated Bleeding Rate (bleeds/subject/year) | 95% CI | Historical Control Group Estimated Bleeding Rate; (bleeds/subject/year)
All | 41 | 0.138 | [0.058; 0.332] | 1.68
< 18 years | 15 | 0.362 | [0.136; 0.963] | 2.00
≥ 18 years | 26 | 0.040 | [0.006; 0.283] | 1.59

Thirty-four (34) of the 41 subjects and an additional 21 new subjects were enrolled in an ongoing second trial. During a total treatment period of 107.5 subject years (mean of 1.95 years per subject), 5 subjects experienced 6 bleeds that required treatment with a FXIII-containing product. The mean annual rate of bleeding episodes that required treatment was determined to be 0.056 per subject year. The age-adjusted rate of bleeding episodes that required treatment during the TRETTEN treatment period was 0.022 per subject year [95% CI:0.0045; 0.1023] with a model-based estimate corresponding to a mean age of 29.5 years. The annual mean bleeding rate in subjects below age 18 was higher compared to that in adults (0.127 versus 0.026 bleeds/subject/year) with some overlap of the respective 95% confidence intervals. Table 6 lists the estimated bleeding rates by age.

Table 6 Estimated Bleeding Rates by Age

Group | N | Estimated Bleeding Rate; (bleeds/subject/year) | 95% CI
All | 55 | 0.056 | [0.025; 0.124]
< 18 years | 16 | 0.127 | [0.048; 0.339]
≥ 18 years | 39 | 0.026 | [0.007; 0.105]

15 REFERENCES

1. Inbal, A., et.al.:Recombinant factor XIII: a safe and novel treatment for congenital factor XIII deficiency, Blood. 2012;119(22): 5111-5117
2. Sharief, LAT., Kadir RA.:Congenital factor XIII deficiency in women: a systemic review of literature, Hemophilia. 2013; 19: e349-e357

16 HOW SUPPLIED/STORAGE AND HANDLING

How Supplied

TRETTEN, Coagulation Factor XIII A-Subunit (Recombinant), is supplied as a white, lyophilized powder in single-dose vial along with the diluent (Sterile Water for Injection) vial.

The actual amount of TRETTEN in international units (IU) is stated on each carton and vial. TRETTEN and the sterile water vials provided in the package are not made with natural rubber latex.

Presentation | Carton NDC Number | Components NDC Number
2000 - 3125 IU | 0169-7013-01 | - TRETTEN Single-dose Vial [NDC 0169-7113-11] - Sterile Water for Injection Vial [NDC 0169-7000-93]

Storage and Handling

- Store refrigerated at 2°C – 8°C (36°F – 46°F) prior to reconstitution. TRETTEN is stable until the expiration date on the carton and vial label. Do not freeze. Store protected from light.
- Use reconstituted TRETTEN within 3 hours.
- If the reconstituted product is not used immediately, store the solution refrigerated or at room temperature not to exceed 25°C (77°F) for up to 3 hours following reconstitution.

17 PATIENT COUNSELING INFORMATION

- Advise patients to read the FDA-approved patient labeling (Patient Information and Instructions for Use).
- Discuss the signs and symptoms of allergic hypersensitivity reactions, such as urticaria, rash, tightness of the chest, wheezing, hypotension and/or anaphylaxis experienced during or after injection of TRETTEN [see Warnings and Precautions (5.1)].
- Discuss signs and symptoms of thrombosis, such as limb or abdomen swelling and/or pain, chest pain, shortness of breath, loss of sensation or motor power, altered consciousness, vision, or speech [see Warnings and Precautions (5.2)].
- Inform patients that breakthrough bleeding may be the sign and symptom of inhibitor formation [see Warnings and Precautions (5.3)].

License Number: 1261

Patent information: http://novonordisk-us.com/patients/products/product-patents.html

Novo Nordisk® is a registered trademark of Novo Nordisk A/S

TRETTEN® is a registered trademark of Novo Nordisk Health Care AG

© 2020 Novo Nordisk

For Information contact:

Novo Nordisk Inc.

800 Scudders Mill Road

Plainsboro, NJ 08536

Manufactured by:

Novo Nordisk A/S

DK-2880 Bagsvaerd, Denmark

Patient Package Insert

TRETTEN®

Coagulation Factor XIII A-Subunit (Recombinant)

This leaflet summarizes important information about TRETTEN. Please read it carefully before using TRETTEN and each time you get a refill because there may be new information provided. This information does not take the place of talking with your healthcare provider, and it does not include all of the important information about TRETTEN. If you have any questions after reading this, ask your healthcare provider.

What is TRETTEN?

TRETTEN is an injectable medicine used to prevent bleeding in adults and children who have congenital factor XIII (FXIII) A-subunit deficiency. TRETTEN is man-made and does not contain animal or human materials.

Who should not use TRETTEN?

You should not use TRETTEN if you have ever had allergic (hypersensitivity) reactions, including severe, whole body reaction (anaphylaxis) to TRETTEN or any of the ingredients.

What should I tell my healthcare provider before TRETTEN is given?

Tell your healthcare provider about all of your medical conditions, including:

- If you are pregnant, think you may be pregnant or planning to become pregnant. It is not known if TRETTEN can harm you or your unborn baby.
- Labor and Delivery: It is not known if TRETTEN is safe and effective during labor and delivery.
- Breast feeding: It is not known if TRETTEN passes into your breast milk.
- If you have a history of blood clots.

Tell your healthcare provider about all of the medicines you take, including all prescription and non-prescription medicines such as over-the-counter medicines, supplements, or herbal remedies.

How is TRETTEN given?

TRETTEN is given as an injection into your vein (intravenous injection). These injections are given once a month. Your dose will depend on your body weight. Use the dose that your healthcare provider has prescribed for you based on your weight.

Before injecting TRETTEN, it must be dissolved (reconstituted) using the sterile water that is provided in the package. Throw away any TRETTEN left in the vial after you inject your dose because it may become unsterile.

What are the possible side effects of TRETTEN?

Call your healthcare provider or go to the emergency department right away if you have any of the following symptoms after using TRETTEN:

- Signs of allergic reaction including
  - shortness of breath
  - rash
  - itching (pruritus)
  - redness of the skin (erythema)
  - fainting/dizziness
- Signs of a blood clot including pain, swelling, warmth, redness, or a lump in your legs or arms, chest pain, or sudden severe headache and/or loss of consciousness or function
- Unexpected bleeding

Other possible side effects may include:

- pain in your arms or legs
- headache
- pain at the injection site

These are not all the possible side effects of TRETTEN. Tell your healthcare provider about any side effect that bothers you or that does not go away. You can also report side effects to the Food and Drug Administration (FDA) at 1-800-FDA-1088.

How should I store TRETTEN?

It is important to store TRETTEN correctly.

Before preparing TRETTEN for injection
Keep TRETTEN in a refrigerator at 36°F to 46°F (2°C to 8°C) and in the original package in order to protect it from light. Do not freeze TRETTEN.
After preparing TRETTEN for injection (reconstituted)

Use TRETTEN immediately after it is dissolved (reconstituted) using the sterile water provided in the package.
If you cannot inject it immediately, either leave TRETTEN at room temperature not above 25°C (77°F) or put
TRETTEN in the refrigerator at 36°F to 46°F (2°C to 8°C) for no more than 3 hours. After more than 3 hours, DO
NOT USE IT—THROW IT AWAY.
TRETTEN does not contain a preservative. Do not store TRETTEN in the syringe or placed in the freezer.

What else should I know about TRETTEN?

Do not use TRETTEN for a condition for which it is not prescribed. Do not share TRETTEN with other people, even if they have the same symptoms that you have.

Talk to your healthcare provider if you would like more information.

TRETTEN ingredients include:

- Coagulation Factor XIII A-Subunit (Recombinant)
- Sodium Chloride
- Sucrose
- Polysorbate 20
- L-Histidine

TRETTEN and the sterile water vials provided in the package are not made with natural rubber latex.

This Patient Package Insert has been approved by the US Food and Drug Administration

Revised: 12/2013

Version: 1

Novo Nordisk® is a registered trademark of Novo Nordisk A/S

TRETTEN® is a registered trademark of Novo Nordisk Health Care AG

© 2013 Novo Nordisk

For Information contact:

Novo Nordisk Inc.

800 Scudders Mill Road

Plainsboro, NJ 08536

www.novonordisk-us.com

1-844-TRETTEN

Manufactured by:

Novo Nordisk A/S

DK-2880 Bagsvaerd, Denmark

Instructions for Use

TRETTEN®

Coagulation Factor XIII A-Subunit (Recombinant)

(For intravenous use only)

READ THESE INSTRUCTIONS CAREFULLY BEFORE USING TRETTEN®.

Do not attempt to do an infusion yourself unless you have been taught by your healthcare provider or hemophilia center.

Always follow the specific instructions given by your healthcare provider. The steps listed below are general guidelines for using TRETTEN®. If you are unsure of this procedure, please call your healthcare provider before using.

Always wash your hands and ensure that the area around you is clean.

When you prepare and inject medication directly into the veins, it is important to use a clean and germ free (aseptic) technique. Improper technique can introduce germs that can infect the blood.

Your healthcare provider will prescribe the dose that you should take.

TRETTEN® is supplied as a powder. Before injection (administration) it must be mixed (reconstituted) with the sterile water supplied in a separate vial. The mixed TRETTEN® must be injected into your vein (intravenous injection).

For reconstitution of the TRETTEN® you will need a syringe and sterile alcohol swabs (not included in the package).

Do not open the package until you are ready to use it.

Do not use TRETTEN® if it is expired. Use a new package instead. The expiration date is printed on the outer carton and on the vials.

Do not use TRETTEN® if the contents in the package appear damaged. Use a new package instead.

Single-dose container. Discard unused portion.

Content

The package contains:

• Vial with TRETTEN® powder

• Vial with sterile water (diluent)

• Vial adapter

Reconstitute TRETTEN® using the following procedure

- Take out the number of TRETTEN® packages you need.
- Check the expiry date.
- Check the name on the package, to make sure it contains the correct product.
- Wash your hands and dry them properly using a clean towel or air dry.
- Bring TRETTEN® (white lyophilized powder) and sterile water (diluent) to room temperature, but not above 25°C (77°F).
- Remove the plastic caps from the two vials. If the plastic cap is loose or missing, do not use the vial.
- Wipe the rubber stopper with a sterile alcohol swab and allow it to air dry for a few seconds before use to ensure that it is as germ free as possible.
- Do not touch the rubber stopper with your fingers as this can transfer germs.
- Hold the vial adapter using the protective cap. Remove the protective paper but do not take the vial adapter out of the protective cap. Do not touch the spike on the vial adapter. If the protective paper is not fully sealed or if it is broken, do not use the vial adapter.
- Place the diluent vial on a flat and solid surface.
- Attach the vial adapter to the diluent vial, without taking the vial adapter out of the protective cap as shown in Figure A.
- Once attached, remove the protective cap from the vial adapter by lightly squeezing the protective cap with your thumb and index finger as shown in Figure B.

- Pull back the plunger of the sterile syringe to draw in a volume of 3.2 mL air into the syringe as shown in Figure C.

- Screw the syringe tightly on to the vial adapter on the diluent vial as shown in Figure D.

- Inject the air from the syringe into the diluent vial until resistance is felt. Then hold the syringe with the diluent vial upside down and withdraw 3.2 mL of sterile water into the syringe as shown in Figure E.

- Remove the empty diluent vial from the vial adapter by tipping the syringe and vial adapter as shown in Figure F.

- Attach the syringe with the vial adapter to the powder vial. Hold the syringe slightly tilted with the vial facing downwards.
- Push the plunger slowly to inject all sterile water (3.2 mL) into the powder vial as shown in Figure G.
- Do not inject the sterile water directly on the TRETTEN® powder to avoid foaming.

- Gently swirl the vial until all the powder is dissolved as shown in Figure H. Do not shake the vial.
- The reconstituted TRETTEN® should be a clear and colorless solution.

Reconstituted TRETTEN® should be used immediately. If not used immediately store refrigerated or at room temperature not to exceed 25°C (77°F) for up to 3 hours. Discard after 3 hours.

Do not freeze mixed TRETTEN® solution or store it in syringes.

Keep mixed TRETTEN® solution out of direct light.

To administer a larger dose, reconstitute each additional vial as required using the same procedure with a separate syringe.

Inject the mixed solution

- Keep the plunger pushed all the way in before turning the syringe upside down.
- Pull the plunger slightly downwards to draw the mixed solution into the syringe as shown in Figure I.
- Only withdraw the amount of mixed solution that your doctor has prescribed, using the scale on the syringe.

- Unscrew the syringe from the vial adapter and vial as shown in Figure J.

TRETTEN® is now ready to inject as instructed by your healthcare provider.

- Remember to only use the amount of TRETTEN® prescribed by your healthcare provider.
- Do not infuse any faster than 1-2 mL per minute.

Disposal

- After injection, safely dispose of the syringe, the vial with the vial adapter, any unused TRETTEN® and other waste materials as instructed by your healthcare provider.

For Full Prescribing Information please read the other insert included in this package.

Revised: 06/2020

Manufactured by:

Novo Nordisk A/S

2880 Bagsvaerd, Denmark

License Number: 1261

Version: 2

PACKAGE/LABEL DISPLAY PANEL

NDC 0169-7013-01 LIST: 701301

2500 IU

TRETTEN®

Coagulation Factor XIII A-Subunit (Recombinant)

For intravenous administration only

For human use only. Single dose. Discard unused portion.

Contains no preservative

Rx only

Package/Label Display Panel

NDC 0169-7113-11 LIST: 711311

2500 IU

TRETTEN®

Coagulation Factor XIII A-Subunit (Recombinant)

For intravenous administration only

Store refrigerated at 2-8°C (36-46°F)

Reconstitute with 3.2 mL sterile water for injection only

Rx only

Novo Nordisk Inc.

1-844-TRETTEN

Expiry/Lot/rFXIII IU per vial:

Package/Label Display Panel

NDC 0169-7000-93 LIST: 700093

3.2 mL

Sterile Water for Injection

For reconstitution of TRETTEN®

Coagulation Factor XIII A-Subunit (Recombinant)

Store at 2-25°C (36-77°F)

Novo Nordisk Inc.

1-844-TRETTEN

Expiry/Lot/: